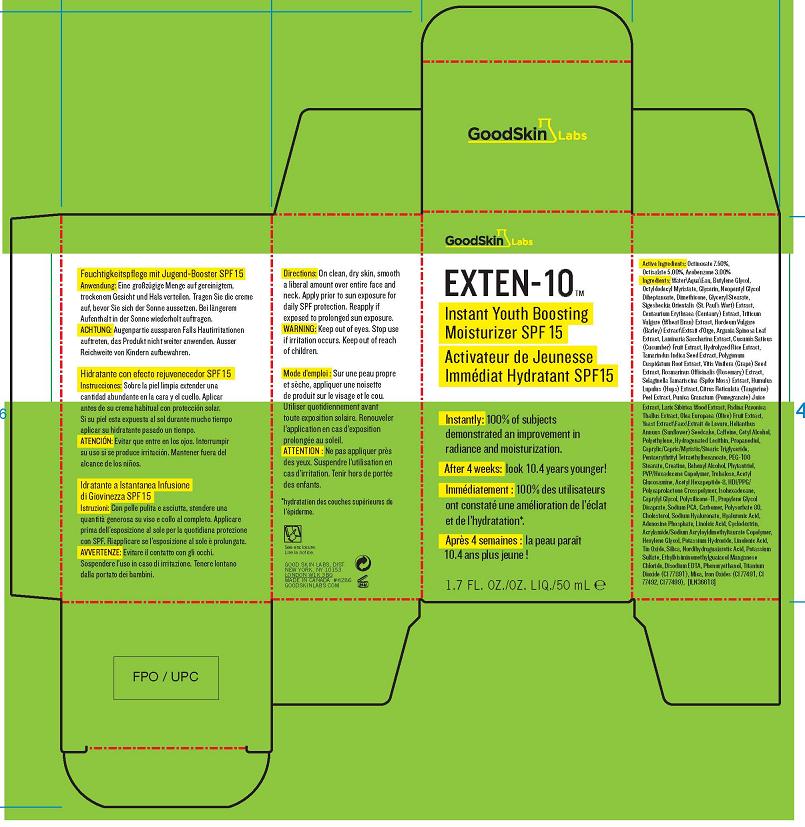 DRUG LABEL: EXTEN-10
NDC: 68758-009 | Form: CREAM
Manufacturer: GOOD SKIN DERMACARE
Category: otc | Type: HUMAN OTC DRUG LABEL
Date: 20100514

ACTIVE INGREDIENTS: OCTINOXATE  7.5 mL/100 mL; OCTISALATE 5.00 mL/100 mL; AVOBENZONE 3.0 mL/100 mL

ACTIVE INGREDIENT

ACTIVE INGREDIENTS: OCTINOXATE 7.50% [] OCTISALATE 5.00% [] AVOBENZONE 3.00%

DOSAGE AND ADMINISTRATION

DIRECTIONS: ON CLEAN DRY SKIN, SMOOTH A LIBERAL AMOUNT OVER ENTIRE FACE AND NECK. APPLY PRIOR TO SUN EXPOSURE FOR DAILY SPF PROTECTION. REAPPLY IF EXPOSED TO PROLONGED SN EXPOSURE

WARNINGS

WARNING: KEEP OUT OF EYES. STOP USE IN IRRITATION OCCURS. KEEP OUT OF REACH OF CHILDREN.

PACKAGE LABEL

PRINCIPAL DISPLAY PANEL:

EXTEN-10
INSTANT YOUTH BOOSTING MOISTURIZER SPF 15
1.7 FL OZ/OZ/LIQ/ 50 ML
GOOD SKIN LABS
GOOD SKIN DERMACARE DIST
NEW YORK, NY 10022